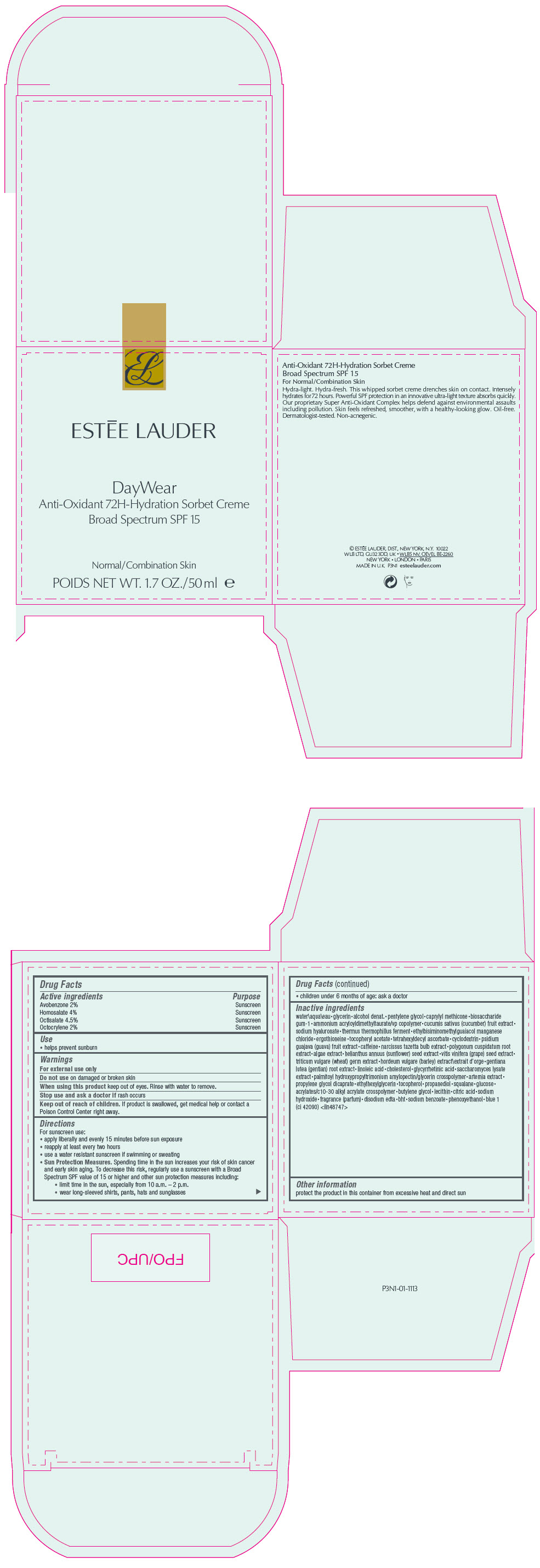 DRUG LABEL: DAYWEAR ANTI OXIDANT 72H-HYDRATION SORBET CREME BROAD SPECTRUM SPF 15
NDC: 11559-055 | Form: CREAM
Manufacturer: ESTEE LAUDER INC
Category: otc | Type: HUMAN OTC DRUG LABEL
Date: 20231121

ACTIVE INGREDIENTS: AVOBENZONE 20 mg/1 mL; HOMOSALATE 40 mg/1 mL; OCTISALATE 45 mg/1 mL; OCTOCRYLENE 20 mg/1 mL
INACTIVE INGREDIENTS: WATER; GLYCERIN; PENTYLENE GLYCOL; BIOSACCHARIDE GUM-1; AMMONIUM ACRYLOYLDIMETHYLTAURATE/VP COPOLYMER; CUCUMBER; HYALURONATE SODIUM; THERMUS THERMOPHILUS LYSATE; ETHYLBISIMINOMETHYLGUAIACOL MANGANESE CHLORIDE; ERGOTHIONEINE; TETRAHEXYLDECYL ASCORBATE; GUAVA; CAFFEINE; HELIANTHUS ANNUUS SEEDCAKE; GRAPE; WHEAT; BARLEY; LINOLEIC ACID; CHOLESTEROL; ENOXOLONE; ETHYLHEXYLGLYCERIN; PROPANEDIOL; SQUALANE; BUTYLENE GLYCOL; CITRIC ACID MONOHYDRATE; SODIUM HYDROXIDE; EDETATE DISODIUM ANHYDROUS; BUTYLATED HYDROXYTOLUENE; PHENOXYETHANOL; FD&C BLUE NO. 1; SODIUM BENZOATE; LECITHIN, SOYBEAN; CARBOMER INTERPOLYMER TYPE A (ALLYL SUCROSE CROSSLINKED); GLUCOSE 1,6-BISPHOSPHATE; TOCOPHEROL; BRINE SHRIMP; TRIMETHYLPENTANEDIOL/ADIPIC ACID/GLYCERIN CROSSPOLYMER (25000 MPA.S); SACCHAROMYCES LYSATE; GENTIANA LUTEA ROOT; AGAR, UNSPECIFIED; REYNOUTRIA JAPONICA ROOT; NARCISSUS TAZETTA BULB; .BETA.-CYCLODEXTRIN SULFOBUTYL ETHER; .ALPHA.-TOCOPHEROL ACETATE; CAPRYLYL TRISILOXANE; ALCOHOL

DAYWEAR ANTI OXIDANT 72H-HYDRATION SORBET CREME BROAD SPECTRUM SPF 15

Drug Facts

ACTIVE INGREDIENT

Active ingredients | Purpose
Avobenzone 2.0% | Sunscreen
Homosalate 4.0% | Sunscreen
Octisalate 4.5% | Sunscreen
Octocrylene 2.0% | Sunscreen

Use

- helps prevent sunburn

Warnings

For external use only

Do not use on damaged or broken skin

When using this product keep out of eyes. Rinse with water to remove.

Stop use and ask a doctor if rash occurs

Keep out of reach of children. If product is swallowed, get medical help or contact a Poison Control Center right away.

Directions

For sunscreen use:

- apply liberally and evenly 15 minutes before sun exposure
- reapply at least every two hours
- use a water resistant sunscreen if swimming or sweating
- Sun Protection Measures. Spending time in the sun increases your risk of skin cancer and early skin aging. To decrease this risk, regularly use a sunscreen with a Broad Spectrum SPF value of 15 or higher and other sun protection measures including:
  - limit time in the sun, especially from 10 a.m. – 2 p.m.
  - wear long-sleeved shirts, pants, hats and sunglasses
  - children under 6 months of age: ask a doctor

Inactive ingredients

water\aqua\eau•glycerin•alcohol denat.•pentylene glycol•caprylyl methicone•biosaccharide gum-1•ammonium acryloyldimethyltaurate/vp copolymer•cucumis sativus (cucumber) fruit extract•sodium hyaluronate•thermus thermophillus ferment•ethylbisiminomethylguaiacol manganese chloride•ergothioneine•tocopheryl acetate•tetrahexyldecyl ascorbate•cyclodextrin•psidium guajava (guava) fruit extract•caffeine•narcissus tazetta bulb extract•polygonum cuspidatum root extract•algae extract•helianthus annuus (sunflower) seed extract•vitis vinifera (grape) seed extract•triticum vulgare (wheat) germ extract•hordeum vulgare (barley) extract\extrait d'orge•gentiana lutea (gentian) root extract•linoleic acid•cholesterol•glycyrrhetinic acid•saccharomyces lysate extract•palmitoyl hydroxypropyltrimonium amylopectin/glycerin crosspolymer•artemia extract•propylene glycol dicaprate•ethylhexylglycerin•tocopherol•propanediol•squalane•glucose•acrylates/c10-30 alkyl acrylate crosspolymer•butylene glycol•lecithin•citric acid•sodium hydroxide•fragrance (parfum)•disodium edta•bht•sodium benzoate•phenoxyethanol•blue 1 (ci 42090) <iln48747>

Other information

protect the product in this container from excessive heat and direct sun

PRINCIPAL DISPLAY PANEL - 50 ml Jar Carton

ESTĒE LAUDER

DayWear
Anti-Oxidant 72H-Hydration Sorbet Creme
Broad Spectrum SPF 15

Normal/Combination Skin

POIDS NET WT. 1.7 OZ./50 ml e